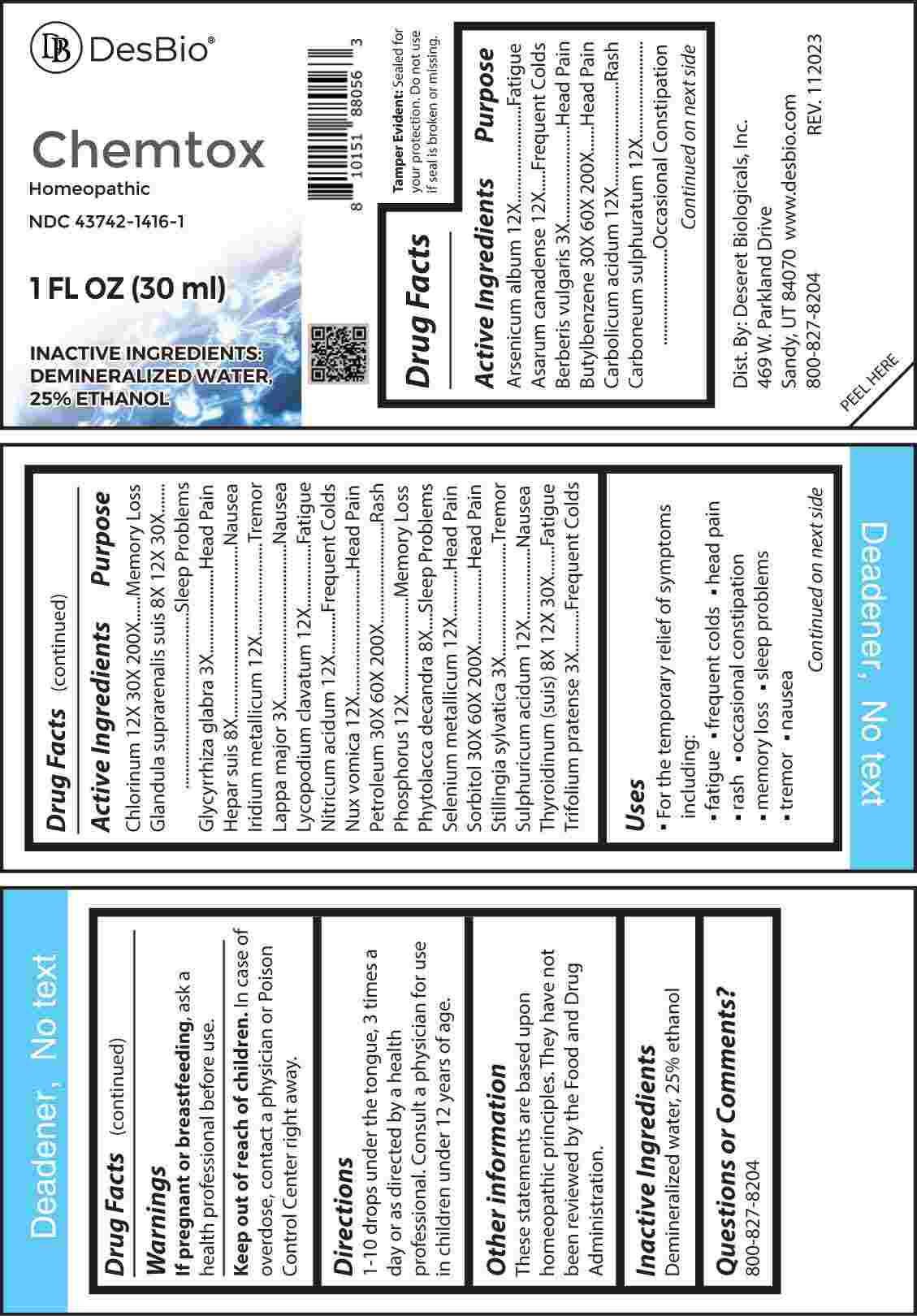 DRUG LABEL: Chemtox
NDC: 43742-1416 | Form: LIQUID
Manufacturer: Deseret Biologicals, Inc.
Category: homeopathic | Type: HUMAN OTC DRUG LABEL
Date: 20240306

ACTIVE INGREDIENTS: BERBERIS VULGARIS ROOT BARK 3 [hp_X]/1 mL; GLYCYRRHIZA GLABRA 3 [hp_X]/1 mL; ARCTIUM LAPPA ROOT 3 [hp_X]/1 mL; STILLINGIA SYLVATICA ROOT 3 [hp_X]/1 mL; TRIFOLIUM PRATENSE FLOWER 3 [hp_X]/1 mL; PORK LIVER 8 [hp_X]/1 mL; PHYTOLACCA AMERICANA ROOT 8 [hp_X]/1 mL; SUS SCROFA ADRENAL GLAND 8 [hp_X]/1 mL; SUS SCROFA THYROID 8 [hp_X]/1 mL; ARSENIC TRIOXIDE 12 [hp_X]/1 mL; ASARUM CANADENSE ROOT 12 [hp_X]/1 mL; PHENOL 12 [hp_X]/1 mL; CARBON DISULFIDE 12 [hp_X]/1 mL; IRIDIUM 12 [hp_X]/1 mL; LYCOPODIUM CLAVATUM SPORE 12 [hp_X]/1 mL; NITRIC ACID 12 [hp_X]/1 mL; STRYCHNOS NUX-VOMICA SEED 12 [hp_X]/1 mL; PHOSPHORUS 12 [hp_X]/1 mL; SELENIUM 12 [hp_X]/1 mL; SULFURIC ACID 12 [hp_X]/1 mL; CHLORINE 12 [hp_X]/1 mL; BUTYLBENZENE 30 [hp_X]/1 mL; KEROSENE 30 [hp_X]/1 mL; SORBITOL 30 [hp_X]/1 mL
INACTIVE INGREDIENTS: WATER; ALCOHOL

DRUG FACTS:

ACTIVE INGREDIENTS:

Arsenicum Album 12X, Asarum Canadense 12X, Berberis Vulgaris 3X, Butylbenzene 30X, 60X, 200X, Carbolicum Acidum 12X, Carboneum Sulphuratum 12X, Chlorinum 12X, 30X, 200X, Glandula Suprarenalis Suis 8X, 12X, 30X, Glycyrrhiza Glabra 3X, Hepar Suis 8X, Iridium Metallicum 12X, Lappa Major 3X, Lycopodium Clavatum 12X, Nitricum Acidum 12X, Nux Vomica 12X, Petroleum 30X, 60X, 200X, Phosphorus 12X, Phytolacca Decandra 8X, Selenium Metallicum 12X, Sorbitol 30X, 60X, 200X, Stillingia Sylvatica 3X, Sulphuricum Acidum 12X, Thyroidinum (Suis) 8X, 12X, 30X, Trifolium Pratense 3X.

PURPOSE:

Arsenicum Album - Fatigue, Asarum Canadense – Frequent Colds, Berberis Vulgaris – Head Pain, Butylbenzene – Head Pain, Carbolicum Acidum - Rash, Carboneum Sulphuratum – Occasional Constipation, Chlorinum – Memory Loss, Glandula Suprarenalis Suis – Sleep Problems, Glycyrrhiza Glabra – Head Pain, Hepar Suis - Nausea, Iridium Metallicum - Tremor, Lappa Major - Nausea, Lycopodium Clavatum - Fatigue, Nitricum Acidum – Frequent Colds, Nux Vomica – Head Pain, Petroleum - Rash, Phosphorus – Memory Loss, Phytolacca Decandra – Sleep Problems, Selenium Metallicum – Head Pain, Sorbitol – Head Pain, Stillingia Sylvatica - Tremor, Sulphuricum Acidum - Nausea, Thyroidinum (Suis) - Fatigue, Trifolium Pratense – Frequent Colds.

USES:

• For the temporary relief of symptoms including:

• fatigue • frequent colds • head pain • rash • occasional constipation

• memory loss • sleep problems • tremor • nausea

These statements are based upon homeopathic principles. They have not been reviewed by the Food and Drug Administration.

WARNINGS:

If pregnant or breast-feeding, ask a health professional before use.

Keep out of reach of children. In case of overdose, contact a physician or Poison Control Center right away.

Tamper Evident: Sealed for your protection. Do not use if seal is broken or missing.

KEEP OUT OF REACH OF CHILDREN:

In case of overdose, contact a physician or Poison Control Center right away.

DIRECTIONS:

1-10 drops under the tongue, 3 times a day or as directed by a health professional. Consult a physician for use in children under 12 years of age.

INACTIVE INGREDIENTS:

Demineralized water, 25% ethanol

QUESTIONS:

Dist. By: Deseret Biologicals, Inc.
469 W. Parkland Drive
Sandy, UT 84070

www.desbio.com

800-827-8204

PACKAGE LABEL DISPLAY:

Des Bio

Chemtox

Homeopathic

NDC 43742-1416-1

1 FL OZ (30 ml)